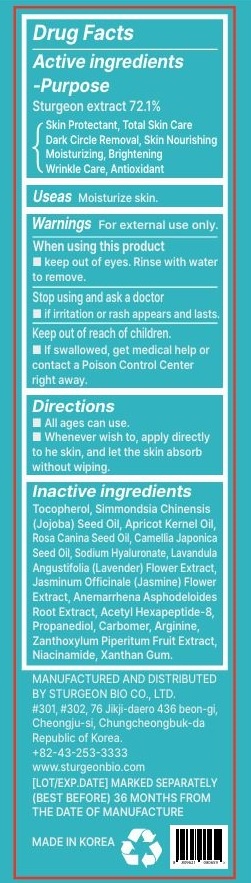 DRUG LABEL: The Zoeun Omega Serum
NDC: 83636-131 | Form: GEL
Manufacturer: Sturgeonbio Co.,Ltd.
Category: otc | Type: HUMAN OTC DRUG LABEL
Date: 20241207

ACTIVE INGREDIENTS: STURGEON, UNSPECIFIED 72.1 g/100 mL
INACTIVE INGREDIENTS: SIMMONDSIA CHINENSIS (JOJOBA) SEED OIL; JASMINUM OFFICINALE (JASMINE) FLOWER EXTRACT; ANEMARRHENA ASPHODELOIDES ROOT; ZANTHOXYLUM PIPERITUM FRUIT PULP; NIACINAMIDE; PROPANEDIOL; XANTHAN GUM; PRUNUS ARMENIACA SEED; ROSA CANINA SEED OIL; SODIUM HYALURONATE; LAVANDULA ANGUSTIFOLIA (LAVENDER) FLOWER EXTRACT; CAMELLIA JAPONICA SEED OIL; CARBOMER HOMOPOLYMER, UNSPECIFIED TYPE; ARGININE; TOCOPHEROL; ACETYL HEXAPEPTIDE-8

83636-131 The Zoeun Skin Omega

Active Ingredients

Sturgeon extract

Purposes

Skin Protectant, Total Skin Care Dark Circle Removal, Skin Nourishing Moisturizing, Brightening
Wrinkle Care, Antioxidant

Uses

Skin Moisturizing, Brightening, Wrinkle Care

Warnings

Keep out of reach of children.
If swallowed, get medical help or contact a Poison Control Center right away.

Warnings

Stop using and ask a doctor if irritation or rash appears and lasts.

Warnings

When using this product keep out of eyes. Rinse with water to remove.

Warnings

For external use only.

Directions

• All ages can use.
• Whenever wish to, apply directly to the skin, and let the skin absorb without wiping.

Inactive Ingredients

Tocopherol, Simmondsia Chinensis (Jojoba) Seed Oil, Apricot Kernel Oil, Rosa Canina Seed Oil, Camellia Japonica Seed Oil, Sodium Hyaluronate, Lavandula Angustifolia (Lavender) Flower Extract, Jasminum Officinale (Jasmine) Flower Extract, Anemarrhena Asphodeloides Root Extract, Acetyl Hexapeptide-8, Propanediol, Carbomer, Arginine, Zanthoxylum Piperitum Fruit Extract, Niacinamide, Xanthan Gum.